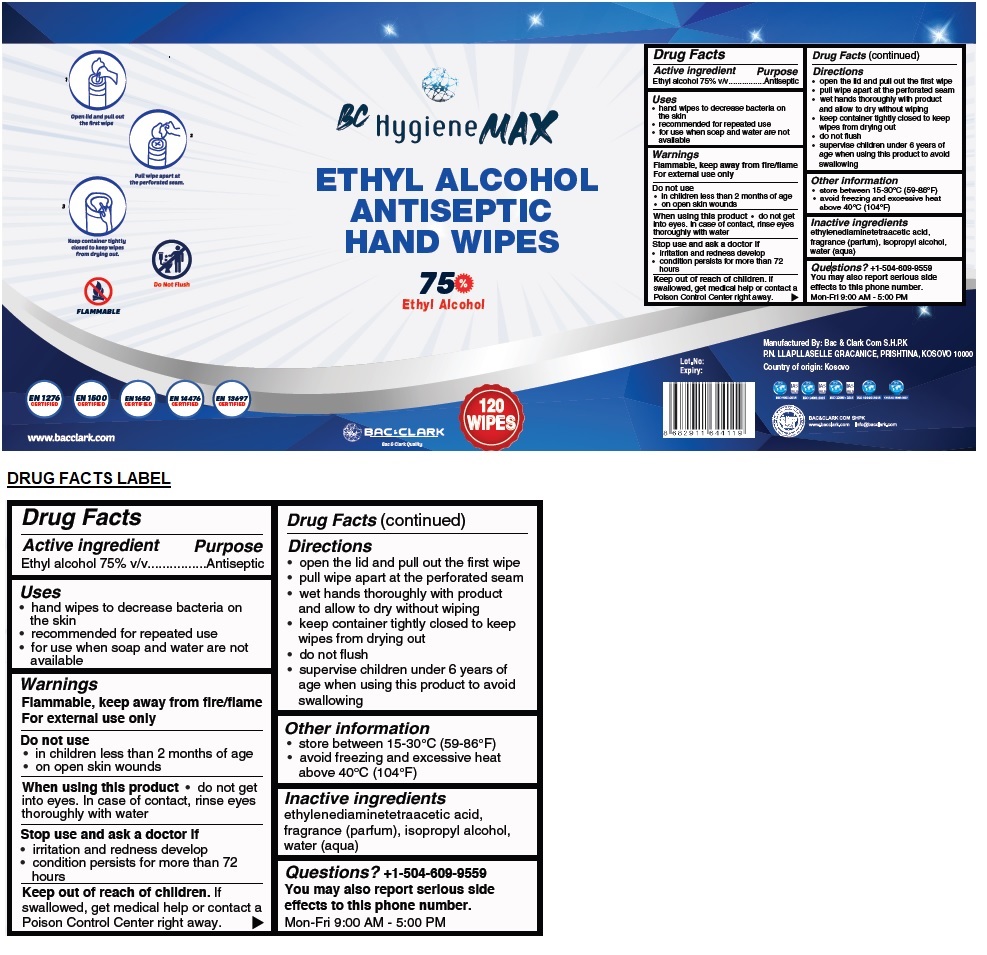 DRUG LABEL: BC Hygiene MAX ETHYL ALCOHOL ANTISEPTIC HAND WIPES
NDC: 81567-101 | Form: CLOTH
Manufacturer: BAC & CLARK COM SH.P.K.
Category: otc | Type: HUMAN OTC DRUG LABEL
Date: 20210212

ACTIVE INGREDIENTS: ALCOHOL 75 mL/100 mL
INACTIVE INGREDIENTS: EDETIC ACID; ISOPROPYL ALCOHOL; WATER

BC Hygiene MAX ETHYL ALCOHOL ANTISEPTIC HAND WIPES

Active ingredient

Ethyl alcohol 75% v/v

Purpose

Antiseptic

Uses

• hand wipes to decrease bacteria on the skin
• recommended for repeated use
• for use when soap and water are not available

Warnings

Flammable, keep away from fire/flame

For external use only

Do not use
• in children less than 2 months of age
• on open skin wounds

When using this product
• do not get into eyes. In case of contact, rinse eyes thoroughly with water

Stop use and ask a doctor if
• irritation and redness develop
• condition persists for more than 72 hours

Keep out of reach of children. If swallowed, get medical help or contact a Poison Control Center right away.

Directions

• open the lid and pull out the first wipe
• pull wipe apart at the perforated seam
• wet hands thoroughly with product and allow to dry without wiping
• keep container tightly closed to keep wipes from drying out
• do not flush
• supervise children under 6 years of age when using this product to avoid swallowing

Other information

• store between 15-30°C (59-86°F)
• avoid freezing and excessive heat above 40°C (104°F)

Inactive ingredients

ethylenediaminetetraacetic acid, fragrance (parfum), isopropyl alcohol, water (aqua)

Questions?

+1-504-609-9559
You may also report serious side effects to this phone number.
Mon-Fri 9:00 AM - 5:00 PM

75% Ethyl Alcohol

Bac & Clark Quality

Manufactured By: Bac & Clark Com S.H.P.K
P.N. LLAPLLASELLE GRACANICE, PRISHTINA, KOSOVO 10000

Country of origin: Kosovo

www.bacclark.com